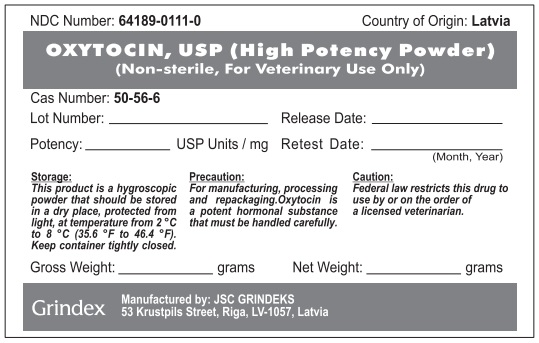 DRUG LABEL: Oxytocin (High Potency Powder)
NDC: 64189-0111 | Form: POWDER
Manufacturer: GRINDEKS Joint Stock Company
Category: other | Type: BULK INGREDIENT - ANIMAL DRUG
Date: 20251216

ACTIVE INGREDIENTS: OXYTOCIN 400000 U/1 g

Oxytocin (High Potency Powder)

WARNINGS AND PRECAUTIONS

Precaution:

For manufacturing, processing and repackaging. Oxytocin is a potent hormonal substance that must be handled carefully.

Caution:

Federal law restricts this drug to use by or on the order of a licensed veterinarian.

Storage:

This product is a hygroscopic powder that should be stored in a dry place, protected from light, at temperature from 2°C to 8°C (35.6°F to 46.4°F). Keep container tightly closed.

PACKAGE LABEL

NDC Number: 64189-0111-0 Country of Origin: Latvia

OXYTOCIN, USP (High Potency Powder)

(Non-sterile, For Veterinary Use Only)

Cas Number: 50-56-6

Lot Number:_____________ Release Date:__________

Potency:__________USP Units / mg Retest Date:___________ (Month, Year)

Storage: This product is a hygroscopic powder that should be stored in a dry place, protected from light, at temperature from 2 °C to 8 °C (35.6 °F to 46.4 °F). Keep container tightly closed.

Precaution: For manufacturing, processing and repackaging. Oxytocin is a potent hormonal substance that must be handled carefully.

Caution: Federal law restricts this drug to use by or on the order of a licensed veterinarian.

Gross Weight:_____________ grams Net Weight:____________ grams

Grindex

Manufactured by: JSC GRINDEKS

53 Krustpils Street, Riga, LV-1057, Latvia